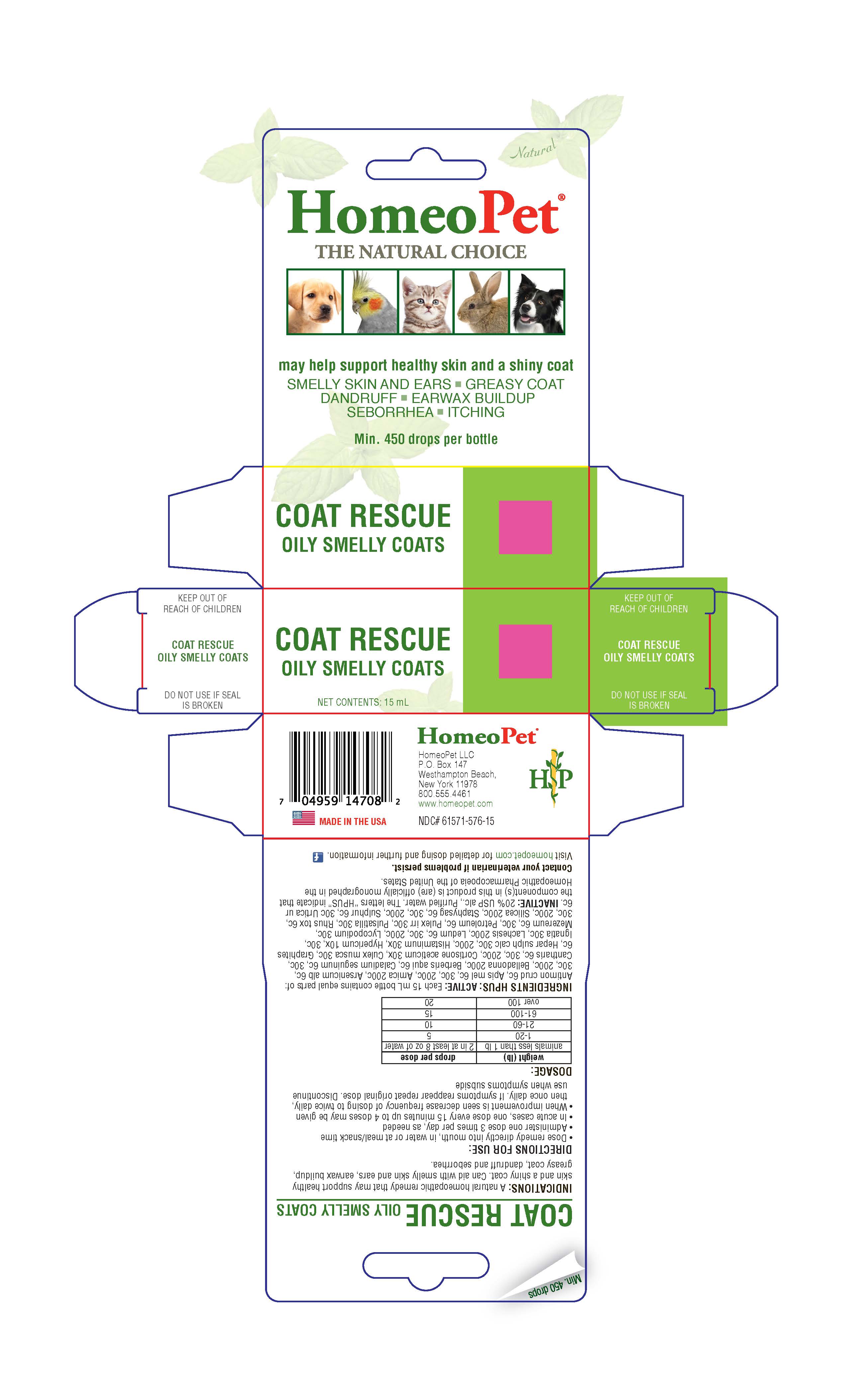 DRUG LABEL: Coat Rescue
NDC: 61571-576 | Form: LIQUID
Manufacturer: HomeoPet, LLC
Category: homeopathic | Type: OTC ANIMAL DRUG LABEL
Date: 20211028

ACTIVE INGREDIENTS: PULEX IRRITANS 30 [hp_C]/15 mL; TOXICODENDRON PUBESCENS LEAF 6 [hp_C]/15 mL; SULFUR 6 [hp_C]/15 mL; URTICA URENS 6 [hp_C]/15 mL; ANTIMONY TRISULFIDE 6 [hp_C]/15 mL; ARNICA MONTANA 200 [hp_C]/15 mL; APIS MELLIFERA 6 [hp_C]/15 mL; ARSENIC TRIOXIDE 6 [hp_C]/15 mL; ATROPA BELLADONNA 200 [hp_C]/15 mL; BERBERIS AQUIFOLIUM ROOT BARK 6 [hp_C]/15 mL; DIEFFENBACHIA SEGUINE 6 [hp_C]/15 mL; LYTTA VESICATORIA 6 [hp_C]/15 mL; CORTISONE ACETATE 30 [hp_X]/15 mL; CULEX PIPIENS 30 [hp_C]/15 mL; GRAPHITE 6 [hp_C]/15 mL; CALCIUM SULFIDE 30 [hp_C]/15 mL; HISTAMINE DIHYDROCHLORIDE 30 [hp_X]/15 mL; HYPERICUM PERFORATUM 10 [hp_X]/15 mL; STRYCHNOS IGNATII SEED 30 [hp_C]/15 mL; LACHESIS MUTA VENOM 200 [hp_C]/15 mL; LEDUM PALUSTRE TWIG 6 [hp_C]/15 mL; LYCOPODIUM CLAVATUM SPORE 30 [hp_C]/15 mL; DAPHNE MEZEREUM BARK 6 [hp_C]/15 mL; LIQUID PETROLEUM 6 [hp_C]/15 mL; ANEMONE PRATENSIS 30 [hp_C]/15 mL; SILICON DIOXIDE 200 [hp_C]/15 mL; DELPHINIUM STAPHISAGRIA SEED 6 [hp_C]/15 mL
INACTIVE INGREDIENTS: ALCOHOL; WATER

Coat Rescue

Coat Rescue

Homeopathic remedy provides relief from the symptoms of skin conditions causing smelly skin and ears, dull/greasy coat and dandruff. Also provides relief from dermatitits including that from flea, bug and insect bites. Helps with itching and promotes healing of irritated scabs, sores and hive-like red spots.

Coat Rescue

DIRECTIONS FOR USE:

Dose remedy directly into mouth, in water or at meal/snack time
Administer one dose 3 times per day, as needed
In acute cases, one dose every 15 minutes up to 4 doses may be given
When improvement is seen decrease frequency of dosing to twice daily, then once daily. If symptoms reappear repeat original dose. Discontinue use when symptoms subside

DOSAGE:

weight (lb) | drops per dose
animals less than 1lb | 2 in at least 8oz of water
1-20 | 5
21-60 | 10
61-100 | 15
over 100 | 20

ASK DOCTOR

Contact Veterinarian if problems persist.

Visit homeopet.com for detailed dosing and further information.

ACTIVE INGREDIENT

Ingredients HPUS:
Antimon crud 6c, Arnica 200c, Apis mel 6c, 30c, 200c, Arsenicum alb 6c, 30c, 200c, Berberis aqui 6c, Caladium seguinum 6c, 30c, Cantharis 6c, 30c, 200c, Cortisone aceticum 30x, Culex musca 30c, Graphites 6c, Hepar sulph calc 30c, 200c, Histaminum 30x, Hypericum 10x, 30c, Ignatia 30c, Lachesis 200c, ledum 6c 30c, 200c, Lycopodium 30c, Mezereum 6c, 30c, Petroleum 6c, Pulex irr 30c, Pulsatilla 30c, Rhus tox 6c, 30c, 200c, Silicea 200c, Staphysag 6c, 30c, 200c, Sulphur 6c, 30c, Urtica ur 6c in 20% USP alc. in purified water.

INACTIVE INGREDIENT

Alcohol, Purified Water

Coat Rescue

Shiny Coat and Healthy Skin

smelly skin and ears - greasy coat - dandruff - earwax buildup - seborrhea - itching